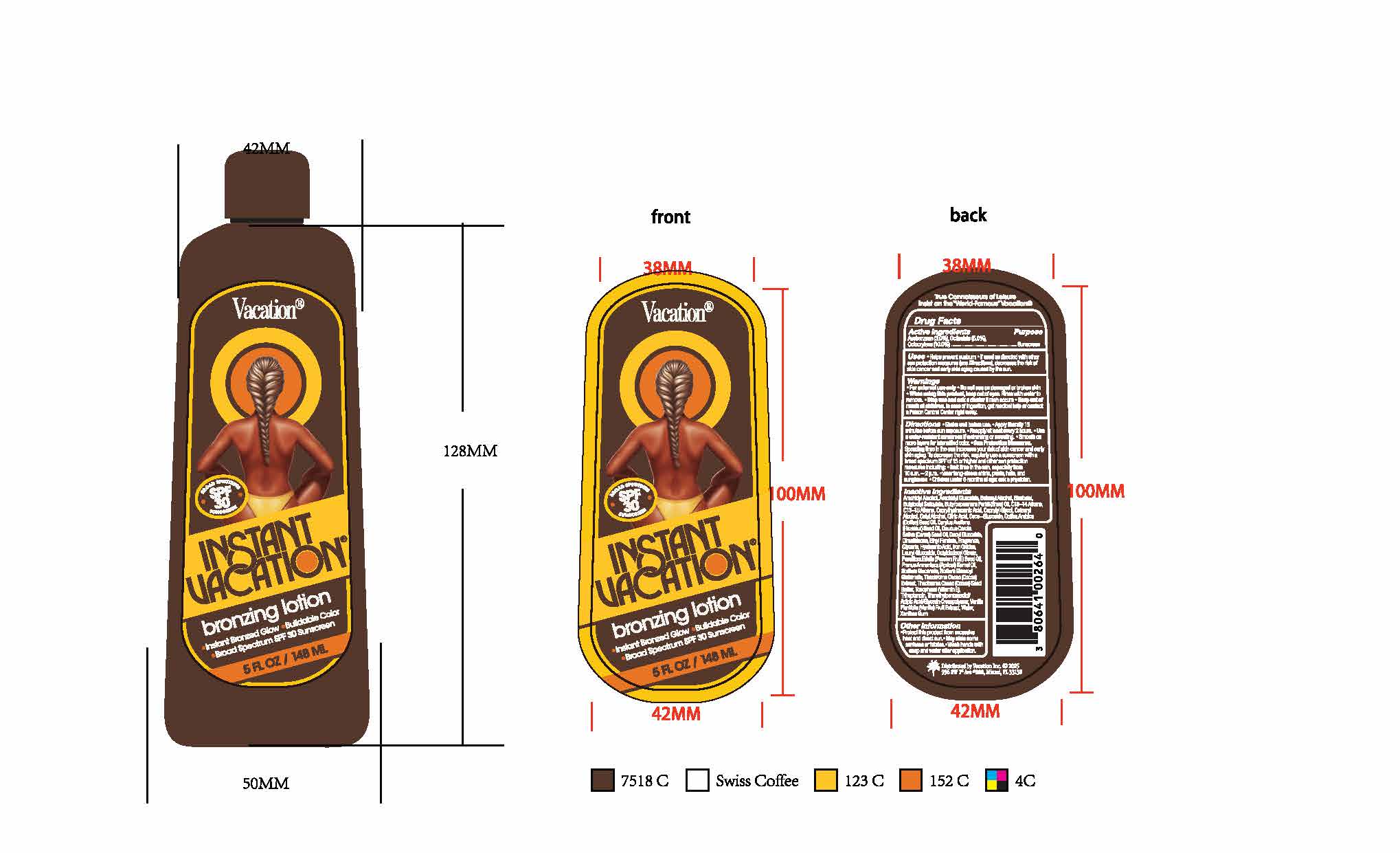 DRUG LABEL: Vacation Instant Browning
NDC: 80641-521 | Form: LOTION
Manufacturer: Vacation Inc.
Category: otc | Type: HUMAN OTC DRUG LABEL
Date: 20250404

ACTIVE INGREDIENTS: AVOBENZONE 2.9 g/100 mL; OCTOCRYLENE 9.5 g/100 mL; OCTISALATE 4.9 g/100 mL
INACTIVE INGREDIENTS: OCTYLDODECYL OLEATE; WATER; C13-15 ALKANE; COCOA BUTTER; TOCOPHEROL; VANILLA PLANIFOLIA OIL; CITRIC ACID MONOHYDRATE; DECYL GLUCOSIDE; BUTYLOCTYL SALICYLATE; BUTYROSPERMUM PARKII (SHEA) BUTTER UNSAPONIFIABLES; CAPRYLHYDROXAMIC ACID; CAPRYLYL GLYCOL; CETOSTEARYL ALCOHOL; CETYL ALCOHOL; COCO GLUCOSIDE; ARABICA COFFEE OIL; EUROPEAN HAZELNUT OIL; DIMETHICONE; ETHYL FERULATE; GLYCERIN; LAURYL GLUCOSIDE; PASSIFLORA EDULIS SEED OIL; TRIHEPTANOIN; SODIUM GLUCONATE; APRICOT SEED OIL; SODIUM STEAROYL GLUTAMATE; HYALURONIC ACID; XANTHAN GUM; ARACHIDYL ALCOHOL; CARROT SEED OIL; BISABOLOL; HELIANTHUS ANNUUS (SUNFLOWER) SEED OIL; TRIMETHYLPENTANEDIOL/ADIPIC ACID/GLYCERIN CROSSPOLYMER (25000 MPA.S); BETA-SITOSTEROL; SQUALENE; BEHENYL ALCOHOL

Vacation Instant Browning Lotion

Dosage and administration

Apply liberally 15 minutes before sun exposure.

Reapply at least every 2 hours.

Use water-resistent sunscreen if swimming or sweating

Warnings

For external use only

Do not use on damaged or broken skin

When using this product, keep out of reach of eyes. Rinse with water to remove.

Stop use and ask a doctor if rash occurs

In case of ingestion, get medical help or contact a Poison Control Center right away

Inactives

OCTISALATE, OCTOCRYLENE, ACETYL L-TYROSINE, LEVOMENOL, MAGNESIUM STEARATE, OCTYLDODECYL OLEATE, WATER, C13-15 ALKANE, PROPANEDIOL, COCOA BUTTER, TOCOPHEROL, VANILLA PLANIFOLIA OIL, DOCOSANOL, DECYL GLUCOSIDE, SODIUM METABISULFITE, PORPHYRIDIUM PURPUREUM, ALCOHOL, BUTYLOCTYL SALICYLATE, BUTYROSPERMUM PARKII (SHEA) BUTTER UNSAPONIFIABLES, CAPRYLHYDROXAMIC ACID, CAPRYLYL GLYCOL, CETOSTEARYL ALCOHOL, CETYL ALCOHOL, CITRIC ACID MONOHYDRATE, COCO GLUCOSIDE, ARABICA COFFEE OIL, EUROPEAN HAZELNUT OIL, DIHYDROXYACETONE, DIMETHICONE, ETHYLENE BRASSYLATE, ETHYL FERULATE, GLYCERIN, FERRIC OXIDE RED, LAURYL GLUCOSIDE, PASSIFLORA EDULIS SEED OIL, CHASTE TREE

Indications and Usage

Helps prevent sunburn

If used as directed with other sun protection measures (see Directions), decreases the risk of skin cancer and early skin agin caused by the sun.

Keep out of reach of children

Keep out of reach of childen

In case of ingestion, get medical help or contact a Poison Control Center right away

Purpose

Sunscreen